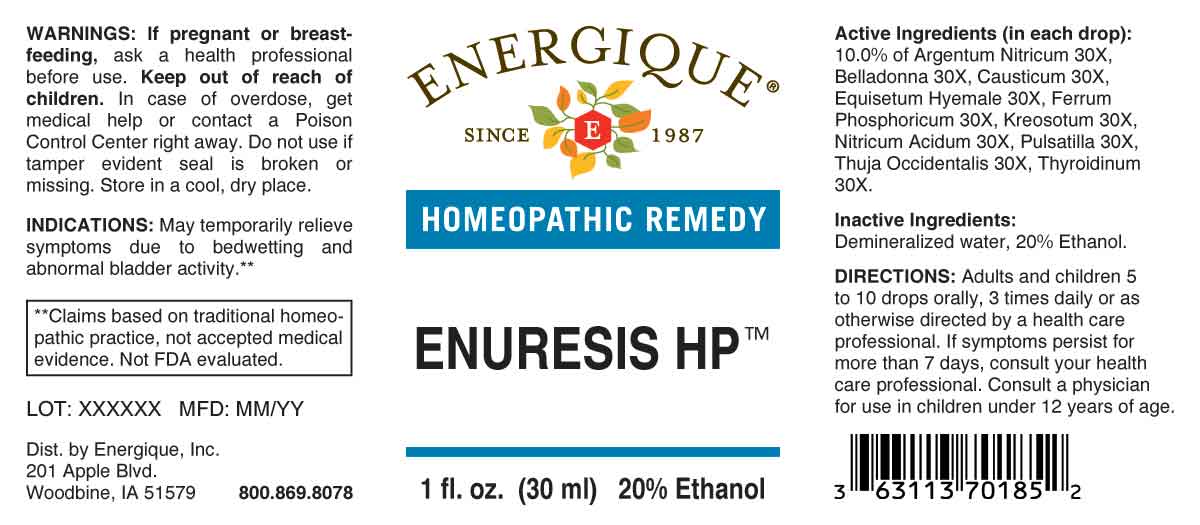 DRUG LABEL: Enuresis
NDC: 44911-0153 | Form: LIQUID
Manufacturer: Energique, Inc.
Category: homeopathic | Type: HUMAN OTC DRUG LABEL
Date: 20230824

ACTIVE INGREDIENTS: SILVER NITRATE 30 [hp_X]/1 mL; ATROPA BELLADONNA 30 [hp_X]/1 mL; CAUSTICUM 30 [hp_X]/1 mL; EQUISETUM HYEMALE WHOLE 30 [hp_X]/1 mL; FERROSOFERRIC PHOSPHATE 30 [hp_X]/1 mL; WOOD CREOSOTE 30 [hp_X]/1 mL; NITRIC ACID 30 [hp_X]/1 mL; PULSATILLA PRATENSIS WHOLE 30 [hp_X]/1 mL; THUJA OCCIDENTALIS LEAFY TWIG 30 [hp_X]/1 mL; THYROID 30 [hp_X]/1 mL
INACTIVE INGREDIENTS: WATER; ALCOHOL

DRUG FACTS:

ACTIVE INGREDIENTS:

(in each drop): 10.0% of Argentum Nitricum 30X, Belladonna 30X, Causticum 30X, Equisetum Hyemale 30X, Ferrum Phosphoricum 30X, Kreosotum 30X, Nitricum Acidum 30X, Pulsatilla 30X, Thuja Occidentalis 30X, Thyroidinum 30X.

INDICATIONS:

May temporarily relieve symptoms due to bedwetting and abnormal bladder activity.**

**Claims based on traditional homeopathic practice, not accepted medical evidence. Not FDA evaluated.

WARNINGS:

If pregnant or breast-feeding, ask a health professional before use.

Keep out of reach of children. In case of overdose, get medical help or contact a Poison Control Center right away.

Do not use if tamper evident seal is broken or missing. Store in a cool, dry place.

KEEP OUT OF REACH OF CHILDREN:

In case of overdose, get medical help or contact a Poison Control Center right away.

DIRECTIONS:

Adults and children 5 to 10 drops orally, 3 times daily or as otherwise directed by a health care professional. If symptoms persist for more than 7 days, consult your health care professional. Consult a physician for use in children under 12 years of age.

INDICATIONS:

May temporarily relieve symptoms due to bedwetting and abnormal bladder activity.**

**Claims based on traditional homeopathic practice, not accepted medical evidence. Not FDA evaluated.

INACTIVE INGREDIENTS:

Demineralized water, 20% Ethanol.

QUESTIONS:

Dist. by Energique, Inc.

201 Apple Blvd.

Woodbine, IA 51579 800.869.8078

PACKAGE LABEL DISPLAY:

ENERGIQUE

SINCE 1987

HOMEOPATHIC REMEDY

ENURESIS HP

1 fl. oz. (30 ml)